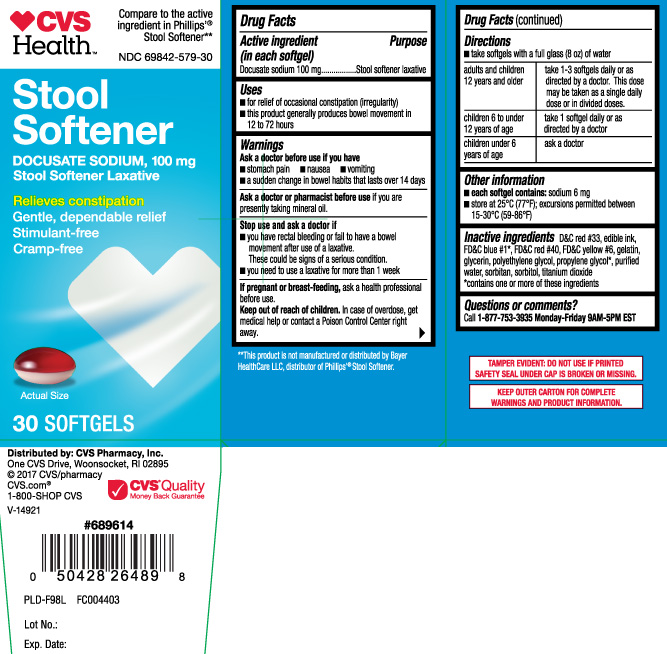 DRUG LABEL: Stool Softener Laxative
NDC: 69842-579 | Form: CAPSULE, LIQUID FILLED
Manufacturer: CVS Pharmacy
Category: otc | Type: HUMAN OTC DRUG LABEL
Date: 20240307

ACTIVE INGREDIENTS: DOCUSATE SODIUM 100 mg/1 1
INACTIVE INGREDIENTS: D&C RED NO. 33; FD&C BLUE NO. 1; FD&C RED NO. 40; FD&C YELLOW NO. 6; GELATIN; GLYCERIN; POLYETHYLENE GLYCOL, UNSPECIFIED; PROPYLENE GLYCOL; WATER; SORBITAN; SORBITOL; TITANIUM DIOXIDE

Drug Facts

Active ingredient (in each softgel)

Docusate sodium 100 mg

Purpose

Stool softener laxative

Uses

- for relief of occasional constipation (irregularity)
- this product generally produces bowel movement in 12 to 72 hours

Warnings

Ask a doctor before use if you have

- stomach pain
- nausea
- vomiting
- a sudden change in bowel habits that lasts over 14 days

Ask a doctor or Pharmacist before use if you are

presently taking mineral oil.

Stop use and ask a doctor if

- you have rectal bleeding or fail to have a bowel movement after use of a laxative. These could be signs of a serious condition.
- you need to use a laxative for more than 1 week

If pregnant or breast-feeding,

ask a health professional before use.

Keep out of reach of children.

In case of overdose, get medical help or contact a Poison Control Center right away.

Directions

- take softgels with a full glass (8 oz) of water

adults and children 12 years and older | take 1-3 softgels daily or as directed by a doctor. This dose may be taken as a single daily dose or in divided doses
children 6 to under 12 years of age | take 1 softgel daily or as directed by a doctor
children under 6 years of age | ask a doctor

Other information

- each softgel contains: sodium 6 mg
- store at 25ºC (77ºF); excursions permitted between 15-30ºC (59-86ºF)

Inactive ingredients

D&C red #33*, edible ink, FD&C blue #1*, FD&C red #40, FD&C yellow #6, gelatin, glycerin, polyethylene glycol, propylene glycol*, purified water, sorbitan, sorbitol, titanium dioxide

*contains one or more of these ingredients

Questions or comments?

Call 1-877-753-3935 Monday-Friday 9AM-5PM EST

Principal Display Panel

Compare to the active ingredient in Phillips'® Stool Softener**

Stool Softener

DOCUSATE SODIUM, 100 mg

Stool Softener Laxative

Relieves constipation

Gentle, dependable relief

Stimulant-free

Cramp-free

SOFTGELS

**This product is not manufactured or distributed by Bayer HealthCare LLC, distributor of Phillips'® Stool Softener.

TAMPER EVIDENT: DO NOT USE IF PRINTED SAFETY SEAL UNDER CAP IS BROKEN OR MISSING.

KEEP OUTER CARTON FOR COMPLETE WARNINGS AND PRODUCT INFORMATION.

Distributed by: CVS Pharmacy, Inc.

One CVS Drive, Woonsocket, RI 02895

CVS.com®

Product Label

CVS HEALTH Stool Softener Laxative